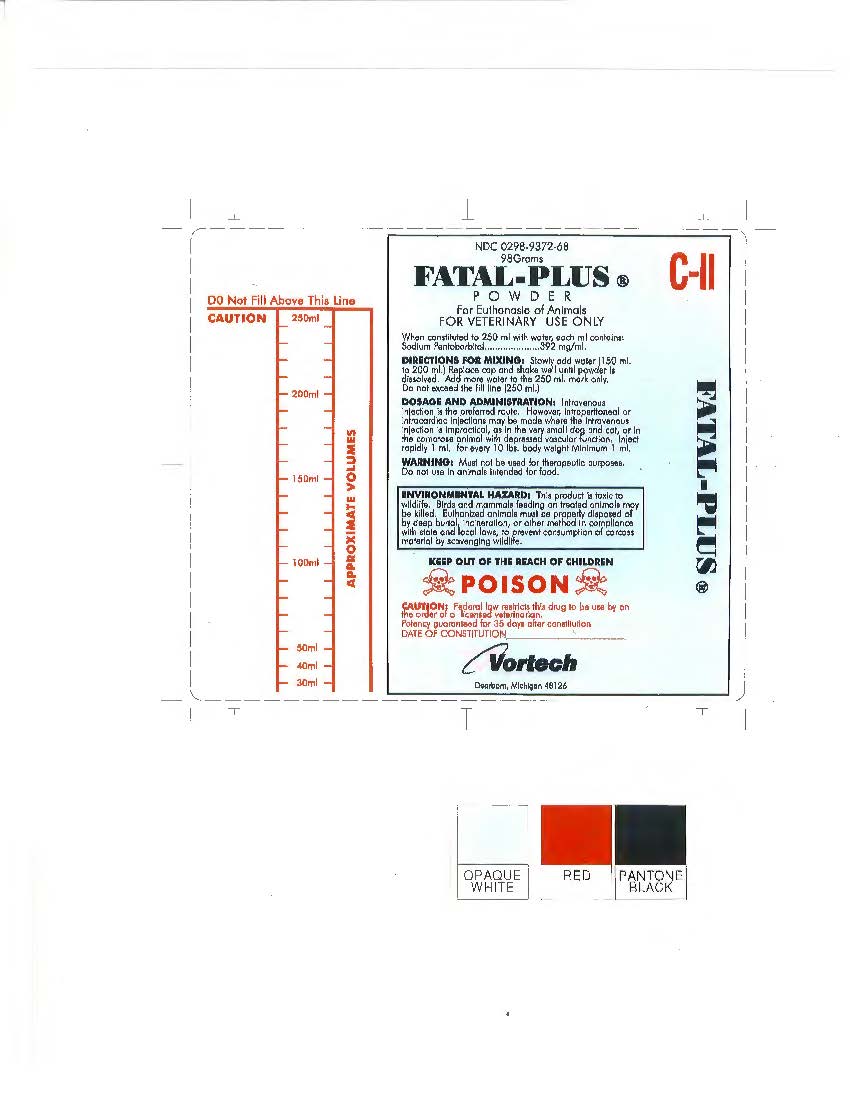 DRUG LABEL: Fatal-Plus Powder
                        
NDC: 0298-9372 | Form: INJECTION, SOLUTION
Manufacturer: Vortech Pharmaceuticals, Ltd.
Category: animal | Type: PRESCRIPTION ANIMAL DRUG LABEL
Date: 20161221
DEA Schedule: CII

ACTIVE INGREDIENTS: Pentobarbital Sodium 392 mg/1 mL

Fatal-Plus Powder

Description

Fatal-Plus Powder

Pentobarbital Sodium - 98 grams

FOR VETERINARY USE ONLY

For Euthanasia of Animals

DIRECTIONS FOR MIXING:

Slowly add water (150 mL to 200 mL).

Replace cap and shake well until powder is dissolved.

Add more water to the 250 mL mark only.

Do not exceed the fill line (250 mL).

DOSAGE AND ADMINISTRATION:

Intravenous injection is the preferred route. However, intraperitoneal or intracardiac injections may be made where the intravenous injection is impractical, as in the very small dog and cat, or in the comatose animal with depressed vascular function. Inject rapidly 1 mL for every 10 lbs. body weight Minimum 1 mL.

WARNING: Must not be used for therapeutic purposes. Do not use in animals intended for food.
ENVIRONMENTAL HAZARD:

This product is toxic to wildlife. Birds and mammals feeding on treated animals may be killed. Birds and mammals feeding on treated animals may be killed. Euthanized animals must be properly disposed of by deep burial, incineration, or other method in compliance with state and local laws, to prevent consumption of carcass material by scavenging wildlife.

CAUTION: Federal law restricts this drug to use by or on the order of a licensed veterinarian.

POISON: KEEP OUT OF THE REACH OF CHILDREN

Principle Display Panel

Fatal-Plus Powder - NDC: 0298-9372-68

Pentobarbital Sodium - 98 grams

FOR VETERINARY USE ONLY

For Euthanasia of Animals

DIRECTIONS FOR MIXING:

Slowly add water (150 mL to 200 mL).

Replace cap and shake well until powder is dissolved.

Add more water to the 250 mL mark only.

Do not exceed the fill line (250 mL).

DOSAGE AND ADMINISTRATION:

Intravenous injection is the preferred route. However, intraperitoneal or intracardiac injections may be made where the intravenous injection is impractical, as in the very small dog and cat, or in the comatose animal with depressed vascular function. Inject rapidly 1 mL for every 10 lbs. body weight Minimum 1 mL.

WARNING: Must not be used for therapeutic purposes. Do not use in animals intended for food.

ENVIRONMENTAL HAZARD:

This product is toxic to wildlife. Birds and mammals feeding on treated animals may be killed. Birds and mammals feeding on treated animals may be killed. Euthanized animals must be properly disposed of by deep burial, incineration, or other method in compliance with state and local laws, to prevent consumption of carcass material by scavenging wildlife.

CAUTION: Federal law restricts this drug to use by or on the order of a licensed veterinarian.

POISON:

KEEP OUT OF THE REACH OF CHILDREN